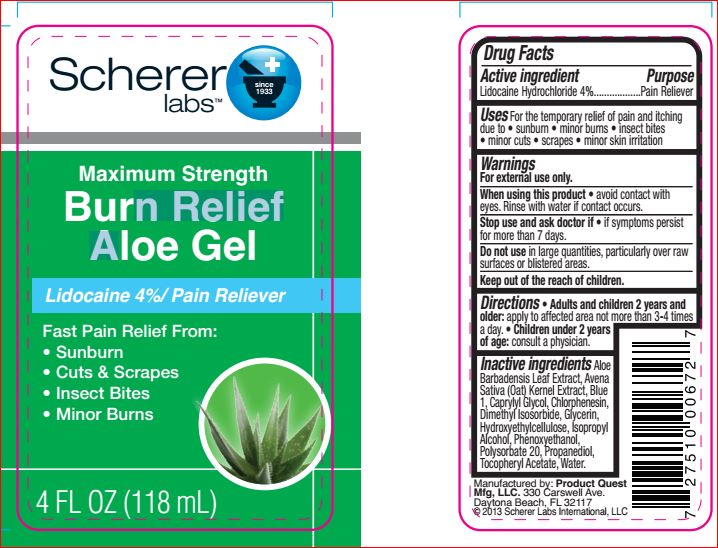 DRUG LABEL: Maximum Strength Burn Relief Aloe Gel
NDC: 64048-5002 | Form: GEL
Manufacturer: Product Quest Mfg.
Category: otc | Type: HUMAN OTC DRUG LABEL
Date: 20180529

ACTIVE INGREDIENTS: Lidocaine Hydrochloride 4 g/100 mL
INACTIVE INGREDIENTS: ALOE VERA LEAF; OAT; FD&C BLUE NO. 1; Caprylyl Glycol; Chlorphenesin; Dimethyl Isosorbide; Glycerin; Isopropyl Alcohol; Phenoxyethanol; Polysorbate 20; Propanediol; .ALPHA.-TOCOPHEROL ACETATE; WATER

Drug Facts

Active ingredients Purpose

Lidocaine Hydrochloride - 4.00% Topical analgesic

Uses

For the temporary relief of pain and itching
due to • sunburn • minor burns • insect bites
• minor cuts • scrapes • minor skin irritation

Warnings
For external use only.
When using this product • avoid contact with
eyes. Rinse with water if contact occurs.
Stop use and ask doctor if • if symptoms persist
for more than 7 days.
Do not use in large quantities, particularly over raw
surfaces or blistered areas.

Directions

• Adults and children 2 years and
older: apply to affected area not more than 3-4 times
a day. • Children under 2 years
of age: consult a physician.

Inactive ingredients

Aloe Barbadensis Leaf Extract, Avena
Sativa (Oat) Kernel Extract, Blue
1, Caprylyl Glycol, Chlorphenesin,
Dimethyl Isosorbide, Glycerin,
Hydroxyethylcellulose, Isopropyl
Alcohol, Phenoxyethanol,
Polysorbate 20, Propanediol,
Tocopheryl Acetate, Water.